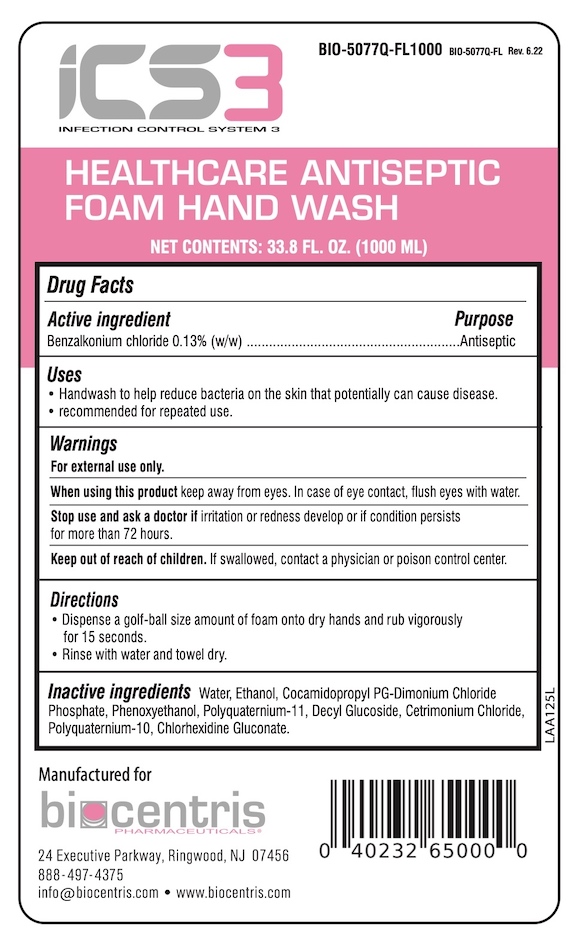 DRUG LABEL: ICS3 Antiseptic Foam Hand Wash
NDC: 81232-165 | Form: LIQUID
Manufacturer: Biocentris Pharmaceuticals, LLC
Category: otc | Type: HUMAN OTC DRUG LABEL
Date: 20220630

ACTIVE INGREDIENTS: BENZALKONIUM CHLORIDE 0.13 g/100 mL
INACTIVE INGREDIENTS: CETRIMONIUM CHLORIDE; CHLORHEXIDINE GLUCONATE; COCAMIDOPROPYL PG-DIMONIUM CHLORIDE PHOSPHATE; DECYL GLUCOSIDE; ALCOHOL; PHENOXYETHANOL; POLYQUATERNIUM-10 (30000 MPA.S AT 2%); POLYQUATERNIUM-11 (1000000 MW); WATER

ICS3 - Antiseptic Foam Hand Wash

Drug Facts

Active ingredient

Benzalkonium chloride 0.13% (w/w)

Purpose

Antiseptic

Uses

- Handwash to help reduce bacteria on the skin that potentially can cause disease.
- recommended for repeated use.

Warnings

For external use only.

When using this product keep away from eyes. In case of eye contact, flush eyes with water.

Stop use and ask a doctor if irritation or redness develop or if condition persists for more than 72 hours.

Keep out of reach of children. If swallowed, contact a physician or poison control center.

Directions

- Dispense a golf ball size amount of foam onto dry hands and rub vigorously for 15 seconds.
- Rinse with water and towel dry.

Inactive ingredients

Water, Ethanol, Cocamidopropyl PG-dimonium Chloride Phosphate, Phenoxyethanol, Polyquarternium 11, Decyl Glucoside, Cetrimonium Chloride, Polyquaternium-10, Chlorhexidine Gluconate

Manufactured for

biocentris PHARMACEUTICALS

24 Executive Parkway, Ringwood, NJ 07456

888-497-7375

info@biocentris.com • www.biocentris.com

PACKAGE LABEL

iCS3®

INFECTION CONTROL SYSTEM 3

HEALTHCARE ANTISEPTIC FOAM HAND WASH

NET CONTENTS 33.8 FL. OZ. (1000 ML)